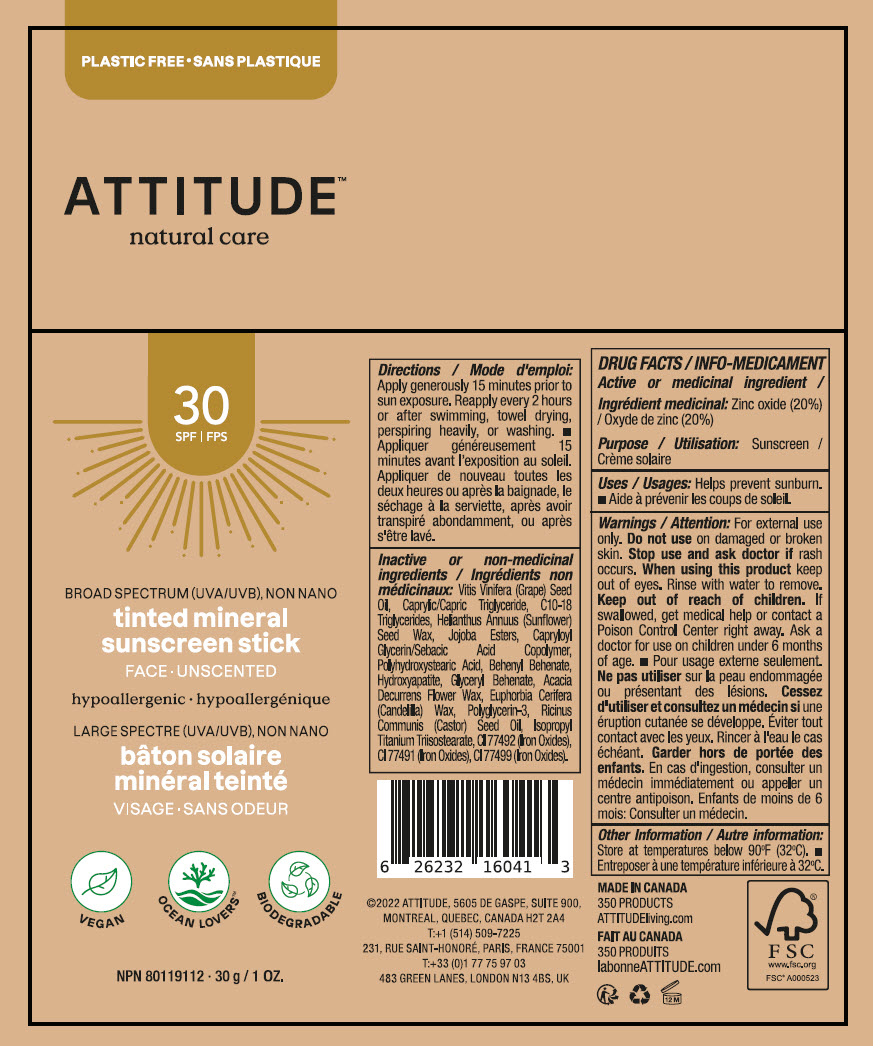 DRUG LABEL: Attitude tinted mineral sunscreen face unscented SPF 30
NDC: 61649-041 | Form: STICK
Manufacturer: Attitude DBA 9055-7588 Québec Inc.
Category: otc | Type: HUMAN OTC DRUG LABEL
Date: 20240328

ACTIVE INGREDIENTS: ZINC OXIDE 20 g/100 g
INACTIVE INGREDIENTS: GRAPE SEED OIL; MEDIUM-CHAIN TRIGLYCERIDES; C10-18 TRIGLYCERIDES; HELIANTHUS ANNUUS SEED WAX; JOJOBA OIL, RANDOMIZED; CAPRYLOYL GLYCERIN/SEBACIC ACID COPOLYMER (2000 MPA.S); POLYHYDROXYSTEARIC ACID (2300 MW); BEHENYL BEHENATE; TRIBASIC CALCIUM PHOSPHATE; ACACIA DECURRENS FLOWER WAX; POLYGLYCERIN-3; CANDELILLA WAX; GLYCERYL MONOBEHENATE; CASTOR OIL; FERRIC OXIDE YELLOW; FERRIC OXIDE RED; FERROSOFERRIC OXIDE; ISOPROPYL TITANIUM TRIISOSTEARATE

Attitude™ tinted mineral sunscreen stick face unscented SPF 30

DRUG FACTS

Active or medicinal ingredient

Zinc oxide (20%)

Purpose

Sunscreen

Uses

Helps prevent sunburn.

Warnings

For external use only.

Do not useon damaged or broken skin.

Stop use and ask doctor ifrash occurs.

WHEN USING

When using this productkeep out of eyes. Rinse with water to remove.

Keep out of reach of children.If swallowed, get medical help or contact a Poison Control Center right away. Ask a doctor for use on children under 6 months of age.

Other Information

Store at temperatures below 90°F (32°C).

Directions

Apply generously 15 minutes prior to sun exposure. Reapply every 2 hours or after swimming, towel drying, perspiring heavily, or washing.

Inactive or non-medicinal ingredients

Vitis Vinifera (Grape) Seed Oil, Caprylic/Capric Triglyceride, C10-18 Triglycerides, Helianthus Annuus (Sunflower) Seed Wax, Jojoba Esters, Capryloyl Glycerin/Sebacic Acid Copolymer, Polyhydroxystearic Acid, Behenyl Behenate, Hydroxyapatite, Glyceryl Behenate, Acacia Decurrens Flower Wax, Euphorbia Cerifera (Candelilla) Wax, Polyglycerin-3, Ricinus Communis (Castor) Seed Oil, Isopropyl Titanium Triisostearate, CI 77492 (Iron Oxides), CI 77491 (Iron Oxides), CI 77499 (Iron Oxides).

PRINCIPAL DISPLAY PANEL - 30 g Tube Label

PLASTIC FREE

ATTITUDE™
natural care

30
SPF

BROAD SPECTRUM (UVA/UVB), NON NANO

tinted mineral
sunscreen stick

FACE ∙ UNSCENTED

hypoallergenic

VEGAN
OCEAN LOVERS™
BIODEGRADABLE

NPN 80119112 ∙ 30 g / 1 OZ.